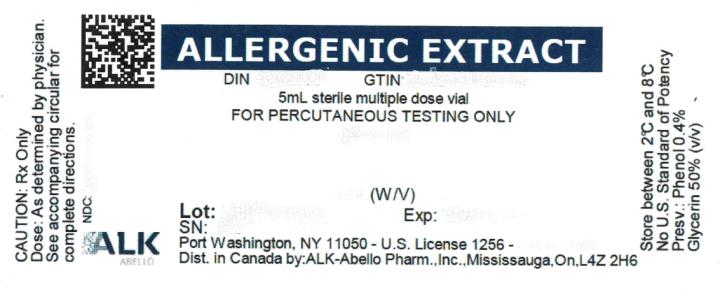 DRUG LABEL: 4 WEED MIX
NDC: 0268-8002 | Form: INJECTION, SOLUTION
Manufacturer: ALK-Abello, Inc.
Category: other | Type: NON-STANDARDIZED ALLERGENIC LABEL
Date: 20230310

ACTIVE INGREDIENTS: XANTHIUM STRUMARIUM POLLEN 0.05 g/1 mL; PLANTAGO LANCEOLATA POLLEN 0.05 g/1 mL; CHENOPODIUM ALBUM POLLEN 0.05 g/1 mL; AMARANTHUS RETROFLEXUS POLLEN 0.05 g/1 mL
INACTIVE INGREDIENTS: SODIUM CHLORIDE 0.009 g/1 mL; SODIUM BICARBONATE 0.0027 g/1 mL; PHENOL 0.004 mL/1 mL; GLYCERIN 0.5 mL/1 mL; HYDROCHLORIC ACID; SODIUM HYDROXIDE

Scratch NonStandardized Products

ALLERGENIC EXTRACTS,

FOR DIAGNOSTIC USE ONLY

DIRECTIONS FOR USE

WARNING

This product is intended for use by physicians who are experienced in the administration of allergenic extracts and the emergency care of anaphylaxis, or for use under the guidance of an allergy specialist.

As with all allergenic extracts, severe systemic reactions may occur. In certain individuals these life-threatening reactions may result in death. Fatalities associated with skin testing have been reported. Patients should be observed for at least 20 - 30 minutes following testing. Emergency measures and adequately trained personnel should be immediately available in the event of a life-threatening reaction.

Patients with unstable asthma or steroid dependent asthmatics and patients with underlying cardiovascular disease are at greater risk to a fatal outcome from a systemic allergic reaction.

Sensitive patients may experience severe anaphlactic reactions resulting in respiratory obstruction, shock, coma and/or death. Adverse events are to be reported to MedWatch (1-800-FDA-1088), Adverse Event Reporting, Food and Drug Administration, 5600 Fishers Lane, Rockville, MD 20852-9787. This product should not be injected intravenously. Patients receiving beta blockers may not be responsive to epinephrine or inhaled bronchodilators. Respiratory obstruction not responding to parenteral or inhaled bronchodilators may require theophylline, oxygen, intubation and the use of life support systems. Parenteral fluid and/or plasma expanders may be utilized for the treatment of shock. Adrenocorticosteroids may be administered parenterally or intravenously. Refer to WARNINGS, PRECAUTIONS, and ADVERSE REACTIONS sections below.

Port Washington, NY 11050

U.S. Government License No. 1256

DESCRIPTION

Sterile diagnostic extracts are supplied in either phenol-saline diluent for Intradermal Testing or in diluent containing glycerin 50% (v/v) for Percutaneous Testing and phenol 0.4% (preservative). Inactive ingredients may include: sodium chloride for isotonicity, glycerin, and sodium bicarbonate as a buffer.

Pollens are individually extracted from pure pollen extracted in a phenol-preserved sodium bicarbonate solution. Short Ragweed and Mixed (Tall and Short) Ragweed extracts are standardized by Antigen E content and so labeled. The Antigen E content of extracts containing Short Ragweed at a concentration more dilute than a weight/volume ratio of 1:10 are obtained by calculating the Antigen E content based on the assay value of more concentrated extract. Pollen extracts are filtered aseptically and after final packaging, they are tested for sterility and safety. Molds are individually extracted from pure powdered inactivated mold source material extracted in phenol preserved saline. Mold extracts are filtered aseptically and after final packaging are tested for sterility and safety.

Molds (fungi) are present in all inhabited places at all seasons of the year; they are so ubiquitous that they are prevalent at times when common allergic pollens and other inhalants are not. In the home and surroundings, molds are found in upholstered furniture, mattresses, drapes, cellar and storage room dust, woolens, leather goods, fruits, meats, cheeses, garden soil and on plants. Spores, mycelial fragments and mold residues are thus inhaled, contacted and ingested continuously.

Foods, miscellaneous inhalants and epidermals are individually extracted in phenol preserved saline or glycerin, filtered aseptically and after final packaging are tested for sterility and safety.

CLINICAL PHARMACOLOGY

Diagnostically (for skin testing) the allergen combines with IgE antibodies fixed to mast cells in the skin. This complexing causes an increase in cellular permeability and degranulation of the mast cells releasing chemical mediators. These mediators (such as histamine) are responsible for a local inflammatory response of wheal and erythema typical of a positive skin test reaction and also, the symptoms commonly associated with allergic disease.^1 The more mediator release, the larger the reaction (wheal and erythema).

INDICATIONS AND USAGE

These products are for diagnostic use only. Diagnostic allergenic extracts are indicated for use in skin testing to establish the clinical relevance of specific allergens to which the patient has been exposed. By measuring skin test response, the physician may assess the degree of sensitivity that patients have to the allergens. For extracts standardized in AU and BAU, see individual directions for use. Allergenic extracts for diagnostic use only of coffee, mosquito, cottonseed, and flaxseed have not been shown by adequate data to be safe and effective for therapeutic use.

CONTRAINDICATIONS

Patients on beta blockers can be non-responsive to beta agonists that may be required to reverse a systemic reaction (also, see boxed WARNING statement and ADVERSE REACTIONS). The physician should carefully weigh the benefit derived from skin testing vs. the risk to the patient should a systemic reaction arise.

Patients with unstable asthma or steroid dependent asthmatics and patients with underlying cardiovascular disease are at greater risk to a fatal outcome from a systemic allergic reaction^2,3. See also PRECAUTIONS and ADVERSE REACTIONS.

WARNINGS

Severe Allergic Reactions:

Patients should always be observed for at least 20 - 30 minutes after skin testing. In the event of a marked systemic reaction such as urticaria, angioedema, wheezing, dyspnea, respiratory obstruction, hypotension, coma and death (see ADVERSE REACTIONS), applications of a tourniquet above the injection site and administration of 0.2 mL to 1 mL (0.01 mg/kg) of epinephrine injection (1:1,000) are recommended. Maximal recommended dose for children between 2 and 12 years of age is 0.5 mL. The tourniquet is then gradually released at 15-minute intervals. Patients under treatment with beta blockers may be refractory to the usual dose of epinephrine.

Volume expanders and vasopressor agents may be required to reverse hypotension, inhalation bronchodilators and parenteral aminophylline may be required to reverse bronchospasm. In case of respiratory obstruction, oxygen and intubation may be necessary. Life-threatening reactions unresponsive to the above may require cardiopulmonary resuscitation.

Anaphylaxis Following False Negative Food Allergen Skin Test Results:

False negative skin test results associated with anaphylaxis from subsequent exposure to the allergen have been reported during postmarketing diagnostic use of some food allergenic extracts. Based on the patient’s clinical history and the index of suspicion, healthcare providers should consider confirming negative skin testing with serologic testing by measuring specific serum IgE or with a medically-supervised oral food challenge.

INFORMATION FOR PATIENTS:

Patients should be instructed to describe any active allergic symptoms such as rhinitis, wheezing, dyspnea, etc. prior to testing. Also, see ADVERSE REACTIONS and WARNINGS Sections.

Patients should always be observed 20 to 30 minutes after testing.

General:

1. In the presence of active symptoms such as rhinitis, wheezing, dyspnea, etc., the indications for skin testing must be weighed carefully against the risk of temporarily aggravating the symptoms by the testing itself. Objective assessment of pulmonary function such as Peak Expiratory Flow Rate (PEFR) before allergen administration and prior to discharge may be useful in unstable asthmatics to reduce the chances of exacerbation of the patient’s asthma. Patients should be instructed to describe any active allergic symptoms as described above prior to skin testing and encouraged to report any late reactions from this testing. Also, see ADVERSE REACTIONS and WARNING sections.
2. Store allergenic extracts between 2°-8°C at all times, even during use.
3. Care must be taken to avoid drawing blood.
  1. For percutaneous testing, if blood is observed, immediately wipe the allergen from the site.
  2. For intradermal skin testing, pull gently on the syringe plunger and note if any blood enters the syringe. If blood is obtained, reposition the needle and repeat before injecting (see DOSAGE AND ADMINISTRATION).
4. Allergenic extracts become less potent with age. Allergenic extracts containing glycerin 50% v/v are relatively stable. Non-glycerinated aqueous extracts, particularly dilute forms as used for intradermal skin testing, have been shown to be extremely unstable. Until such time as stability studies are complete with dilute allergens, new intradermal strength materials should be prepared every few weeks.
5. Use standard aseptic precautions if making dilutions from stock concentrates to intradermal strength.
6. For intradermal testing: Extracts in glycerin 50% v/v must be diluted with a non-glycerinated diluent and must be diluted at least 25-fold to less than 2% glycerin by volume, as glycerin above this level can cause false positive intradermal skin test results.

Pregnancy - Category C:

Animal reproduction studies have not been conducted with allergenic extracts. It is also not known whether allergenic extracts can cause fetal harm when administered to a pregnant woman or can affect reproduction capacity.

Controlled studies of hyposensitization with moderate to high doses of allergenic extracts during conception and all trimesters of pregnancy have failed to demonstrate any risk to the fetus or to the mother^4. However, on the basis of histamine’s known ability to contract the uterine muscle, the release of significant amounts of histamine from allergen exposure to skin test overdose should be avoided on theoretical grounds. Therefore, allergenic extracts should be used cautiously in a pregnant woman and only if clearly needed.

Pediatric Use:

Allergenic extracts for diagnostic use have been given safely in infants and young children. Infants have lower skin test reactivity to histamine, as well as common allergens. Skin test reactivity gradually increases to age 6 and plateaus to age 60. Therefore, small skin test reactions should be anticipated in children under age 6.

Geriatric Use:

Skin test reactivity gradually decreases after age 60. Therefore, smaller skin test reactions should be anticipated in adults over age 60.

Nursing Mothers:

It is not known if allergens administered subcutaneously appear in human milk. Because many drugs are excreted in human milk, caution should be exercised when allergenic extracts are administered to a nursing woman.

Carcinogenesis, mutagenesis, impairment of fertility:

Studies in animals have not been performed.

Drug Interactions:

Drugs can interfere with the performance of skin tests^5.

Antihistamines: Response to mediator (histamine) released by allergens is suppressed by antihistamines. The length of suppression varies and is dependent on individual patient, type of antihistamine and length of time the patient has been on antihistamines. The duration of this suppression may be as little as 24 hours (chlorpheniramine) and can be as long as 40 days (astemizole).

Tricyclic Antidepressants: These exert a potent and sustained decrease of skin reactivity to histamine which may last for a few weeks.

Beta2 Agonists: Oral terbutaline and parenteral ephedrine, in general, have been shown to decrease allergen induced wheal.

Dopamine: Intravenous infusion of dopamine may inhibit skin test responses.

Beta Blocking Agents: Propranolol can significantly increase skin test reactivity.

Other Drugs: Short acting steroids, inhaled beta2 agonists, theophylline and cromolyn do not seem to affect skin test response.

ADVERSE REACTIONS

Fatalities from skin testing in the United States have been extensively reviewed by Lockey.^2 Six fatalities were associated with intradermal testing without previous percutaneous testing, and one was associated with a combination of percutaneous (scratch) and intradermal skin testing. With careful attention to dosage and administration, fatal reactions occur infrequently, but it must be remembered that allergenic extracts are highly potent to sensitive individuals and overdosage could result in anaphylactic symptoms. Therefore, it is imperative that physicians administering allergenic extracts for skin testing understand, and be prepared for the treatment of severe reactions.

Local:

Immediate wheal and erythema reactions are to be expected; but if very large, may be the first manifestation of a systemic reaction. In such cases, immediately wipe the test site(s) with sterile gauze or cotton to remove excess allergen.

Systemic Reactions:

Systemic reactions are characterized by one or more of the following symptoms: sneezing, mild to severe generalized urticaria, itching (other than at the skin test site), extensive or generalized edema, wheezing, asthma, dyspnea, cyanosis, hypotension, syncope, and upper airway obstruction. Symptoms may progress to shock and death. Patients should always be observed for at least 20 - 30 minutes after testing.

Volume expanders and vasopressor agents may be required to reverse hypotension. Inhalational bronchodilators and parenteral aminophylline may be required to reverse bronchospasm. Severe airway obstruction unresponsive to bronchodilator may require tracheal intubation and use of oxygen. In the event of a marked systemic reaction, application of a tourniquet above the injection site and the administration of 0.2 mL to 1.0 mL of epinephrine injection (1:1,000) is recommended. Maximum recommended dose for children between 2 and 12 years of age is 0.3 mL. The tourniquet should not be left in place without loosening for 90 seconds every 15 minutes.

Adverse events should be reported via MedWatch (1-800-FDA-1088), Adverse Event Reporting, Food and Drug Administration, 5600 Fishers Lane, Rockville, MD 20852-9787.

OVERDOSAGE

Signs and symptoms of overdose are typically large local and systemic reactions. For management of overdose reactions, refer to the ADVERSE REACTIONS section above.

DOSAGE AND ADMINISTRATION

Parenteral drug products should be inspected visually for particulate matter and discoloration prior to administration, whenever solution and container permit.

Skin test techniques for immediate (Type I) hypersensitivity testing fall into two major categories: percutaneous, and intracutaneous.

Percutaneous techniques:

For percutaneous testing, in general, skin is scratched, punctured or pricked just before the allergen is applied or through a drop of test allergen. There are several devices available for this technique. Refer to the manufacturer or distributor’s circular for specific directions for their use.

In General:

1. It is recommended that the test areas should be placed no closer than 4 - 5 cm apart to avoid interference of reactions when several tests are applied.
2. Skin test areas should be cleansed with alcohol and air dried.
3. Preferably, the allergen should be placed on the volar surface of the forearm, upper arm, or the patient’s back. The patient should be placed in a comfortable position prior to testing.
4. For scratch testing, a sharp, clean, sterile instrument is used to abrade the skin, but not to draw blood. Each scratch should be about 2 - 4 mm in length. A small drop of extract is placed on the surface of the skin.
5. Prick testing: For prick testing, a sharp, sterile instrument is used to puncture the skin slightly, applying it at a 15 - 20° angle to the skin. The instrument is gently raised, “tenting” the skin until it pops out, generally pricking through the drop of allergen. Do not draw blood.
6. For puncture testing, a sharp, clean, sterile instrument must be used. Puncture the skin, through the drop of allergen, perpendicular to the skin. Do not draw blood.

For all of the above techniques, a separate instrument must be used for each patient; if the instrument is to be used to pass through the allergen, to avoid cross-contamination, a separate instrument is to be used for each allergen. The test should be read in 15 minutes, measuring both wheal size and erythema.

Intracutaneous (intradermal) testing:

General: Intradermal testing is more sensitive than percutaneous testing and its specificity is dependent on dose. Intradermal testing is not intended as an initial screen unless used in highly dilute solutions. Intradermal testing is usually reserved for allergens that have demonstrated either negative or equivocal percutaneous skin test response in the face of positive or unclear history.

Intradermal testing of one allergen in several serial dilutions (beginning with the weakest to the more concentrated dilutions) may also be useful in assessing degree of patient sensitivity for the establishment of a safe starting dose for immunotherapy.

Bulk extracts must be diluted for intradermal testing. Use of Sterile Diluent for Allergenic Extracts or Sterile Diluent for Allergenic Extracts Normal Saline with HSA (albumin saline) is recommended. Dilutions should be made with sterile disposable syringes using aseptic technique. Commonly 10 fold dilutions are used to achieve a desired concentration for intradermal testing and continuation of immunotherapy. For example, transferring 0.5 mL of a 10,000 PNU/mL extract into 4.5 mL of diluent will yield 5 mL of extract at 1,000 PNU/mL. For weight volume products, a 1:100 w/v dilution may be prepared from a 1:10 w/v by transferring 0.5 mL of the 1:10 w/v to 4.5 mL of diluent. Prepare as many additional serial dilutions as necessary to reach the appropriate concentration. As a general rule intradermal strength should begin at no higher than 1/100 to 1/1000 of the percutaneous strength that resulted in a negative skin test reaction.

1. It is recommended that the test areas should be spaced no less than 5 cm apart to avoid interference with adjacent allergen or control.
2. Skin should be cleansed with alcohol and air dried.
3. A sterile 1 mL or 1/2 mL syringe with a 26 - 30 gauge needle should be used. A separate sterile syringe should be used for each extract and each patient.
4. Care should be taken to eliminate air bubbles from the syringe prior to injecting the test dose. It is suggested that not more than 6 - 10 allergens of each different type be used at any one time. Very sensitive patients may show rapid response.
5. The skin is held tensely, and the needle is inserted almost parallel to the skin, beveled side up far enough to cover the beveled portion. Slowly inject sufficient extract to make a small bleb of approximately 5 mm in diameter (0.01 - 0.02 mL).
6. Read the test results in 15 minutes.

Selection of the proper strength for intracutaneous testing: A general rule for the prevention of untoward reactions, particularly in extremely sensitive patients, is to screen by percutaneous methods initially, and begin intradermal testing at a strength not more than 1/100 of a negative or equivocal percutaneous reaction.

Controls:

In both percutaneous and intracutaneous tests, a negative control test with diluent alone should be performed because some patients exhibit dermographia, and/or other non-specific irritant responses.

As a positive control in the evaluation of allergenic skin testing, histamine 1 mg/mL (histamine base) should be used for percutaneous testing, and histamine 0.1 mg/mL (histamine base) should be used for intradermal testing.

Interpretation of results:

Patient’s response is graded on the basis of the size of erythema or wheal.^6 General guidelines follow for percutaneous testing, different devices and/or techniques influence the size of the reaction, therefore it is important to refer to the device manufacturer’s or distributor’s instructions when grading reactions.

Percutaneous (prick or scratch) test:

0 No reaction or less than control.

+ Erythema greater than control, smaller than a nickel (21 mm diameter).

++ Erythema greater than a nickel in diameter, no wheal.

+++ Wheal and erythema without pseudopods.

++++ Wheal and erythema with pseudopods.

Intradermal test:

0 No reaction or less than negative control.

+ 3-4 mm wheal with erythema, or erythema alone larger than a nickel (21 mm diameter).

++ 4-8 mm wheal and erythema, without pseudopods.

+++ Over 8 mm wheal and erythema without pseudopods.

++++ Wheal and erythema with pseudopods.

HOW SUPPLIED

For scratch and prick testing: 5 mL dropper applicator vials in 50% v/v glycerin or 10mL stoppered vial in 50% v/v glycerin. Available individually and in a complete set of the most common allergens. Available in either Protein Nitrogen Units (PNU/mL) or weight to volume (w/v).

For intracutaneous testing: 5 mL sterile vials, aqueous based, individually and in a complete set of the most common allergens. Available in either Protein Nitrogen Units (PNU/mL) or weight to volume (w/v).

Histatrol® Positive skin test control - histamine. 1 mg/mL and 0.1 mg/mL histamine base.

See Product Catalog for specific diagnostic concentrations available.

STORAGE

To maintain stability of allergenic extracts, proper storage conditions are essential. Bulk concentrates and diluted extracts are to be stored at 2º to 8ºC even during use. Bulk or diluted extracts are not to be frozen. Do not use after the expiration date shown on the vial label.

REFERENCES

1. Holgate, S.T., Robinson, C. and Church, M.K. Mediators of immediate hypersensitivity. In Middleton et al: Allergy Principles and Practice, St. Louis, 1988, C.V. Mosby, p 135.
2. Lockey, R.F., et al. Fatalities from immunotherapy (IT) and skin testing (ST). J. Allergy Clin. Immunol. 1987: 79: 660.
3. Reid, M.J. et al. Survey of fatalities from skin testing and immunotherapy. 1985-1989. J. Allergy Clin Immunol. 1993; 92:6.
4. DeBuske L. M. et al. Special problems regarding Allergen Immunotherapy in Immunology and Allergy Clinics of North America, Greenburger, P.A. Ed. February 1992; 145-149.
5. Bousquet, J. In vivo methods for the study of allergy: skin test, techniques and interpretation. In: Middleton et al.: Allergy Principles and Practice 3rd Ed. St. Louis: CV Mosby, 1988:167.
6. Freedman, S.O. Asthma and Allergic Rhinitis II. Clinical Aspects, in Freedman and Gold Clinical Immunology 2nd Ed. New York: Harper & Row, 1976: 131.

Revised February 2023 No. 112S

© ALK-Abelló, Inc.

Distributed in Canada by:
ALK-Abelló Pharmaceuticals, Inc.
#35-151 Brunel Road
Mississauga, Ontario
Canada L4Z 2H6

PRINCIPAL DISPLAY PANEL

ALLERGENIC EXTRACT
DIN 00299987
5mL sterile multiple dose vial
FOR PERCUTANEOUS TESTING ONLY